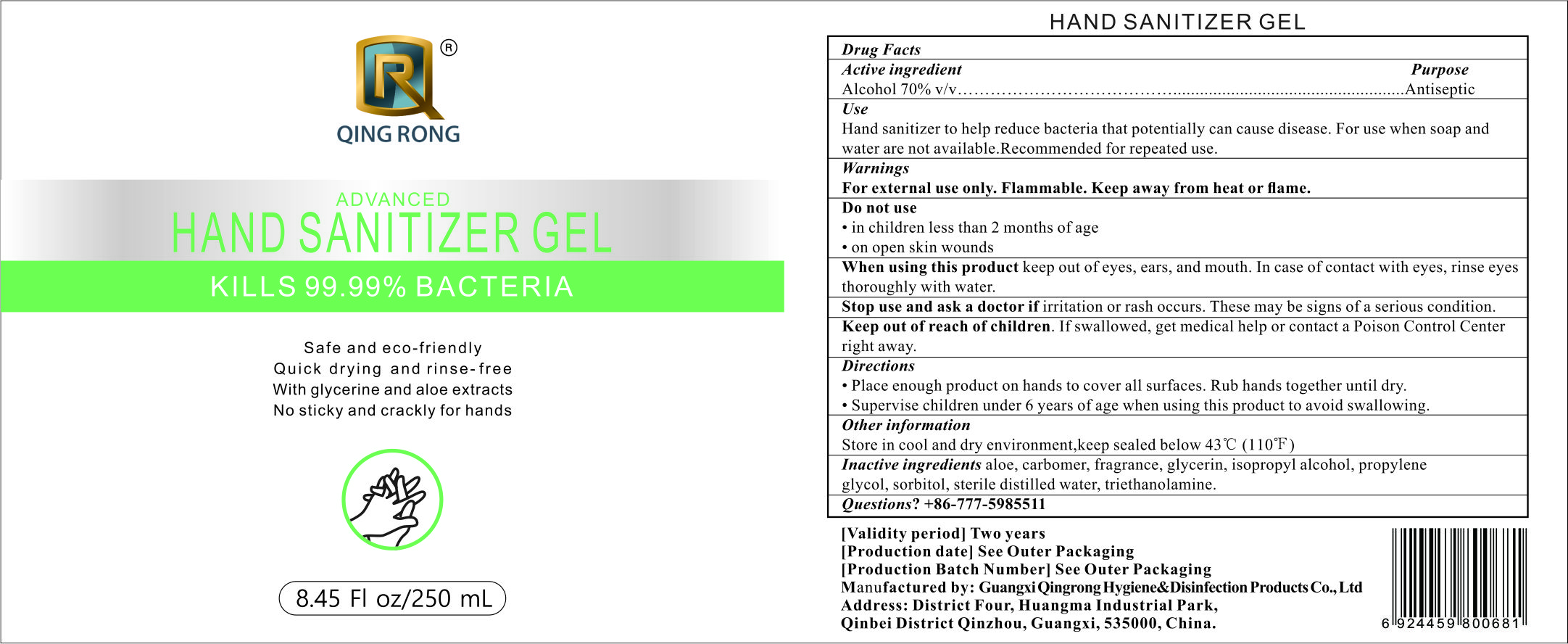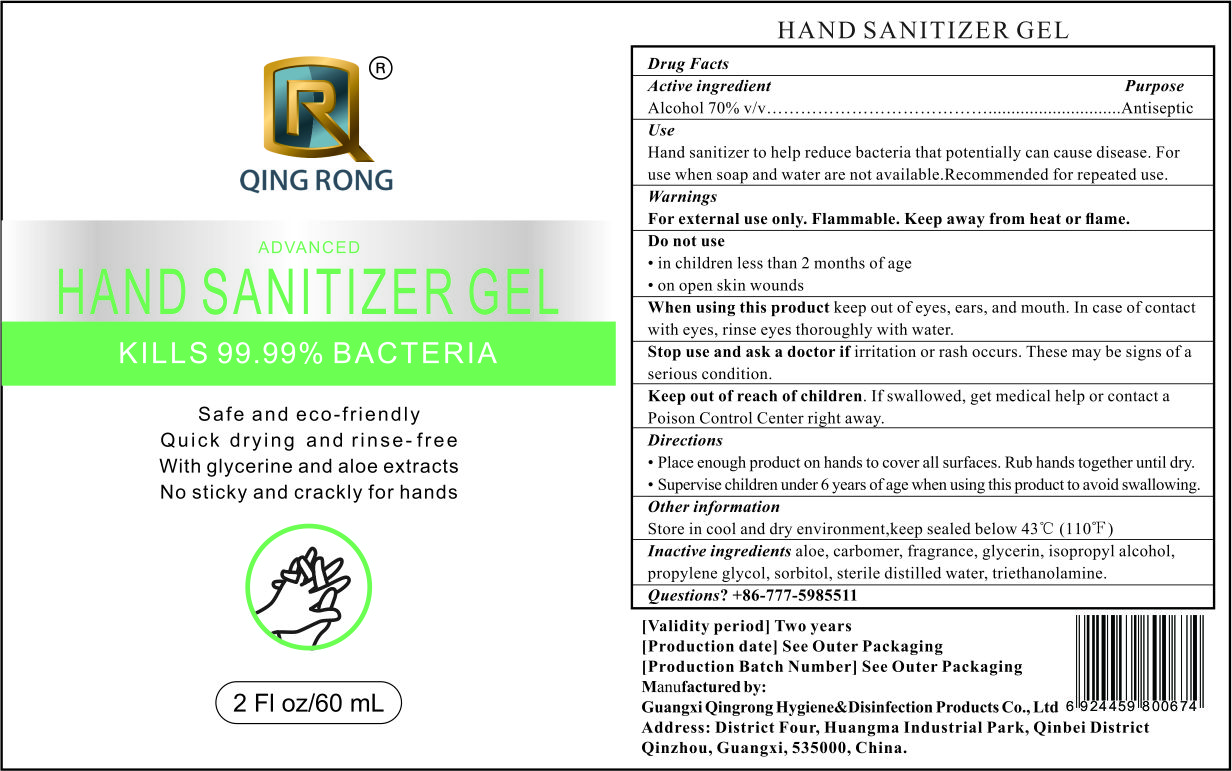 DRUG LABEL: Hand Sanitizer Gel
NDC: 80001-881 | Form: GEL
Manufacturer: Guangxi Qingrong Hygiene&disinfection Products Co.,ltd.
Category: otc | Type: HUMAN OTC DRUG LABEL
Date: 20221208

ACTIVE INGREDIENTS: ALCOHOL 70 mL/100 mL
INACTIVE INGREDIENTS: GLYCERIN 0.5 mL/100 mL; ISOPROPYL ALCOHOL 3 mL/100 mL; WATER 24.15 mL/100 mL; ALOE 1 mL/100 mL; CARBOMER 940 0.24 mL/100 mL; PROPYLENE GLYCOL 0.5 mL/100 mL; TROLAMINE 0.1 mL/100 mL; SORBITOL 0.5 mL/100 mL; FRAGRANCE LAVENDER & CHIA F-153480 0.01 mL/100 mL

Active Ingredient(s)

Alcohol 70% v/v. Purpose: Antiseptic

Purpose

Antiseptic, Hand Sanitizer

Use

Hand Sanitizer to help reduce bacteria that potentially can cause disease. For use when soap and water are not available. Recommended for repeated use.

Warnings

For external use only. Flammable. Keep away from heat or flame

Do not use

- in children less than 2 months of age
- on open skin wounds

When using this product keep out of eyes, ears, and mouth. In case of contact with eyes, rinse eyes thoroughly with water.
Stop use and ask a doctor if irritation or rash occurs. These may be signs of a serious condition.
Keep out of reach of children. If swallowed, get medical help or contact a Poison Control Center right away.

Stop use and ask a doctor if irritation or rash occurs. These may be signs of a serious condition.

Keep out of reach of children. If swallowed, get medical help or contact a Poison Control Center right away.

Directions

- Place enough product on hands to cover all surfaces. Rub hands together until dry.
- Supervise children under 6 years of age when using this product to avoid swallowing.

Other information

Store in cool and dry environment, keep sealed below 43C (110F).

Inactive ingredients

aloe, carbomer, fragrance, glycerin, isopropyl alcohol, propylene glycol, sorbitol, sterile distilled water, triethanolamine.

Package Label - Principal Display Panel

60 mL NDC: 80001-881-06

Package Label - Principal Display Panel

250 mL NDC: 80001-881-25

Package Label - Principal Display Panel

500 mL NDC: 80001-881-50